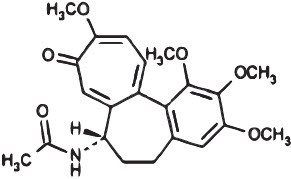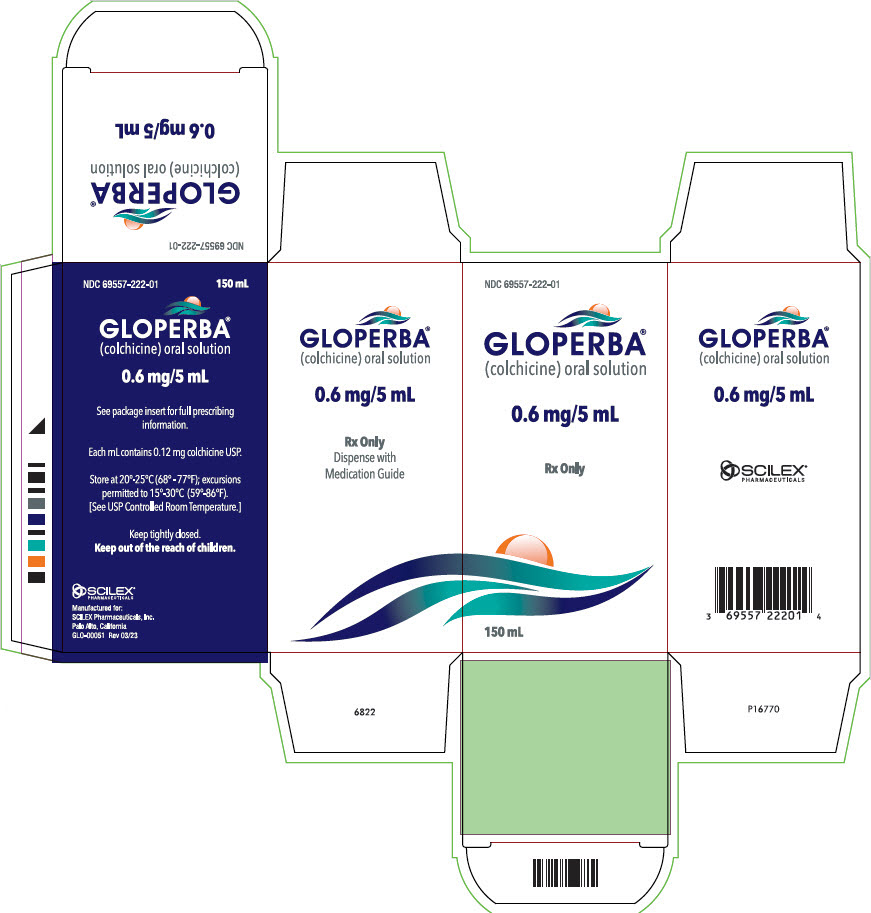 DRUG LABEL: Gloperba
NDC: 69557-222 | Form: SOLUTION
Manufacturer: Scilex Pharmaceuticals Inc.
Category: prescription | Type: HUMAN PRESCRIPTION DRUG LABEL
Date: 20241101

ACTIVE INGREDIENTS: COLCHICINE 0.6 mg/5 mL
INACTIVE INGREDIENTS: BENZYL ALCOHOL; FD&C RED NO. 40; ANHYDROUS CITRIC ACID; SODIUM PHOSPHATE, DIBASIC, UNSPECIFIED FORM; GLYCERIN; PROPYLENE GLYCOL; SUCRALOSE; XANTHAN GUM; WATER; CHERRY

HIGHLIGHTS OF PRESCRIBING INFORMATION

These highlights do not include all the information needed to use GLOPERBA®safely and effectively. See full prescribing information for GLOPERBA®.
GLOPERBA®(colchicine) Oral Solution
Initial U.S. Approval: 1961

1 INDICATIONS AND USAGE

- GLOPERBA is indicated for prophylaxis of gout flares in adults (1).

Limitations of use:

The safety and effectiveness of GLOPERBA for acute treatment of gout flares during prophylaxis has not been studied. GLOPERBA is not an analgesic medication and should not be used to treat pain from other causes (1).

2 DOSAGE AND ADMINISTRATION

0.6 mg (5 mL) once or twice daily. Maximum dose 1.2 mg/day. (2.1)

GLOPERBA is administered orally, without regard to meals (2.1)

3 DOSAGE FORMS AND STRENGTHS

- 0.6 mg/5 mL oral solution (3)

4 CONTRAINDICATIONS

- Patients with renal or hepatic impairment should not be given GLOPERBA in conjunction with drugs that inhibit both CYP3A4 and P-gp (4).
- Patients with both renal and hepatic impairment should not be given GLOPERBA (4).

5 WARNINGS AND PRECAUTIONS

- Fatal overdoseshave been reported with colchicine in adults and children. Keep GLOPERBA out of the reach of children (5.1, 10).
- Blood dyscrasias:myelosuppression, leukopenia, granulocytopenia, thrombocytopenia and aplastic anemia have been reported (5.2).
- Monitor for toxicity and, if present, consider lowering the dose, temporary interruption or discontinuation of colchicine (5.2, 5.3, 5.4, 6, 10).
- Drug interaction with CYP3A4 and P-gp inhibitors:Co-administration of colchicine with dual CYP3A4 and P-gp inhibitors has resulted in life threatening interactions and death (5.3, 7).
- Neuromuscular toxicity:Myotoxicity including rhabdomyolysis may occur, especially in combination with other drugs known to cause this effect. Consider lowering the dose, temporary interruption or discontinuation of GLOPERBA (5.4, 6).

6 ADVERSE REACTIONS

The most commonly reported adverse reactions with colchicine are gastrointestinal symptoms, including diarrhea, nausea, vomiting, and abdominal pain (6).

To report SUSPECTED ADVERSE REACTIONS, contact SCILEX Pharmaceuticals, Inc. at 1-866-SCILEX3 or FDA at 1-800-FDA-1088 (www.fda.gov/medwatch).

7 DRUG INTERACTIONS

- Co-administration of CYP3A4 or P-gp inhibitors or inhibitors of both CYP3A4 and P-gp (e.g., clarithromycin or cyclosporine) have been reported to lead to colchicine toxicity. The potential for drug-drug interactions must be considered prior to and during therapy (7).
- Concomitant use of GLOPERBA and inhibitors of both CYP3A4 and P-gp should be avoided if possible. If co-administration with a CYP3A4 and P-gp inhibitor is required, the patients' dose of colchicine may need to be reduced or interrupted, and the patient should be monitored carefully for colchicine toxicity (7).

8 USE IN SPECIFIC POPULATIONS

- In the presence of renal or hepatic impairment, patients should be monitored closely and dose adjustment should be considered as necessary (8.6, 8.7).
- Females and Males of Reproductive Potential: Advise males that GLOPERBA may rarely and transiently impair fertility (8.3).
- Geriatric Use: The recommended dose of colchicine should be based on renal and hepatic function (8.5, 12.3).

FULL PRESCRIBING INFORMATION

1 INDICATIONS AND USAGE

GLOPERBA®(colchicine) Oral Solution is indicated for prophylaxis of gout flares in adults.

Limitations of use: The safety and effectiveness of GLOPERBA for acute treatment of gout flares during prophylaxis has not been studied.

GLOPERBA is not an analgesic medication and should not be used to treat pain from other causes.

2 DOSAGE AND ADMINISTRATION

2.1 Gout Prophylaxis

For prophylaxis of gout flares, the recommended dosage of GLOPERBA is 0.6 mg (5 mL) once or twice daily. The maximum dose is 1.2 mg/day.

GLOPERBA is administered orally, without regard to meals.

3 DOSAGE FORMS AND STRENGTHS

Ready to use solution for oral administration containing 0.6 mg/5 mL of colchicine. The oral solution is a slightly hazy, red liquid with a cherry odor.

4 CONTRAINDICATIONS

Patients with renal or hepatic impairment should not be given GLOPERBA in conjunction with drugs that inhibit both CYP3A4 and P-gp [see Drug Interactions (7)]. Combining these dual inhibitors with colchicine in patients with renal or hepatic impairment has resulted in life threatening or fatal colchicine toxicity.

Patients with both renal and hepatic impairment should not be given GLOPERBA.

5 WARNINGS AND PRECAUTIONS

5.1 Fatal Overdose

Fatal overdoses, both accidental and intentional, have been reported in adults and children who have ingested colchicine [see Overdosage (10)]. GLOPERBA should be kept out of the reach of children.

5.2 Blood Dyscrasias

Myelosuppression, leukopenia, granulocytopenia, thrombocytopenia, pancytopenia and aplastic anemia have been reported with colchicine used in therapeutic doses.

5.3 Drug Interactions

Because colchicine is a substrate for both the CYP3A4 metabolizing enzyme and the P-gp efflux transporter, inhibition of either of these pathways may lead to colchicine related toxicity. Inhibition of both CYP3A4 and P-gp by dual inhibitors (i.e., clarithromycin) has been reported to produce life threatening or fatal colchicine toxicity due to significant increases in systemic colchicine levels. Therefore, concomitant use of GLOPERBA with inhibitors of both CYP3A4 and P-gp should be avoided. If treatment with colchicine is necessary, a reduced daily dose should be considered and the patient should be closely monitored for colchicine toxicity [see Drug Interactions (7)].

Use of GLOPERBA in conjunction with drugs that inhibit both CYP3A4 and P-gp is contraindicated in patients with renal or hepatic impairment [see Contraindications (4)].

5.4 Neuromuscular Toxicity

Colchicine induced neuromuscular toxicity and rhabdomyolysis have been reported with chronic treatment in therapeutic doses, especially in combination with other drugs known to cause this effect. Patients with impaired renal function and elderly patients, even those with normal renal and hepatic function, are at increased risk. Once colchicine treatment is stopped, the symptoms generally resolve within one week to several months.

6 ADVERSE REACTIONS

Gastrointestinal disorders are the most common adverse reactions with colchicine. These disorders are often the first signs of toxicity and may indicate that the colchicine dose needs to be reduced or therapy stopped. These disorders include diarrhea, nausea, vomiting, and abdominal pain.

Colchicine has been reported to cause neuromuscular toxicity, which may present as muscle pain or weakness [see Warnings and Precautions (5.4)] .

Toxic manifestations associated with colchicine include myelosuppression, disseminated intravascular coagulation and injury to cells in the renal, hepatic, circulatory and central nervous systems. These toxicities most often occur with excessive accumulation or overdosage [see Overdosage (10)] .

The following adverse reactions have been reported with colchicine. These adverse reactions have been generally reversible upon interrupting treatment or lowering the dose of colchicine.

Neurological:sensory motor neuropathy

Dermatological:alopecia, maculopapular rash, purpura, rash

Digestive:abdominal cramping, abdominal pain, diarrhea, lactose intolerance, nausea, vomiting

Hematological:leukopenia, granulocytopenia, thrombocytopenia, pancytopenia, aplastic anemia

Hepatobiliary:elevated AST, elevated ALT

Musculoskeletal:myopathy, elevated CPK, myotonia, muscle weakness, muscle pain, rhabdomyolysis

Reproductive:azoospermia, oligospermia

7 DRUG INTERACTIONS

Colchicine is a substrate of the CYP3A4 metabolizing enzyme and the P-glycoprotein (P-gp) efflux transporter. Fatal drug interactions have been reported when colchicine is administered with clarithromycin, a dual inhibitor of CYP3A4 and P-glycoprotein. Toxicities have also been reported when colchicine is administered with inhibitors of CYP3A4 that may not be potent inhibitors of P-gp (e.g., grapefruit juice, erythromycin, verapamil), or inhibitors of P-gp that may not be potent inhibitors of CYP3A4 (e.g., cyclosporine).

Patients with renal or hepatic impairment should not be given GLOPERBA with drugs that inhibit both CYP3A4 and P-glycoprotein [see Contraindications (4)] . Combining these dual inhibitors with GLOPERBA in patients with renal and hepatic impairment has resulted in life threatening or fatal colchicine toxicity.

Physicians should ensure that patients are suitable candidates for treatment with GLOPERBA and remain alert for signs and symptoms of toxic reactions associated with increased colchicine exposure due to drug interactions. Signs and symptoms of colchicine toxicity should be evaluated promptly and, if toxicity is suspected, consider lowering the dose, interruption or discontinuation of GLOPERBA.

7.1 CYP3A4

The concomitant use of GLOPERBA and CYP3A4 inhibitors (e.g., clarithromycin, ketoconazole, grapefruit juice, erythromycin, verapamil, etc.) should be avoided due to the potential for serious and life threatening toxicity [see Warnings and Precautions (5.3)and Clinical Pharmacology (12.3)] .

If co-administration of GLOPERBA and a CYP3A4 inhibitor is necessary, the dose of GLOPERBA should be adjusted by either reducing the daily dose or reducing the dose frequency, and the patient should be monitored carefully for colchicine toxicity [see Clinical Pharmacology (12.3)].

7.2 P-Glycoprotein

The concomitant use of GLOPERBA and inhibitors of P-glycoprotein (e.g. clarithromycin, ketoconazole, cyclosporine, etc.) should be avoided due to the potential for serious and life threatening toxicity [see Warnings and Precautions (5.3)and Clinical Pharmacology (12.3)] .

If co-administration of GLOPERBA and a P-gp inhibitor is necessary, the dose of GLOPERBA should be adjusted by either reducing the daily dose or reducing the dose frequency, and the patient should be monitored carefully for colchicine toxicity [see Clinical Pharmacology (12.3)] .

7.3 HMG-CoA Reductase Inhibitors and Fibrates

Some drugs such as HMG-CoA reductase inhibitors and fibrates may increase the risk of myopathy when combined with GLOPERBA. Complaints of muscle pain or weakness could be an indication to check serum creatinine kinase levels for signs of myopathy.

7.4 Drug Interaction Studies

Two pharmacokinetic studies evaluated the effects of co-administration of posaconazole (300 mg QD), ciprofloxacin (500 mg BID), amlodipine (5 to 10 mg QD), and carvedilol (20 to 40 mg QD) on the systemic levels of colchicine.

GLOPERBA can be administered with amlodipine, carvedilol, and ciprofloxacin at the tested doses without a need for dose adjustment. However, the results should not be extrapolated to other co-administered drugs. Colchicine plasma levels were markedly elevated when GLOPERBA was co-administered with posaconazole. The recommended dose of GLOPERBA when co-administered with posaconazole is 0.24 mg (2 mL).

8 USE IN SPECIFIC POPULATIONS

8.1 Pregnancy

Risk Summary

Available human data from published literature on colchicine use in pregnancy over several decades have not identified any drug associated risks for major birth defects, miscarriage, or adverse maternal or fetal outcomes (see Data). Although animal reproduction and development studies were not conducted with GLOPERBA, published animal reproduction and development studies indicate that colchicine causes embryofetal toxicity and altered postnatal development at exposures within or above the clinical therapeutic range.

The estimated background risk of major birth defects and miscarriage for the indicated population is unknown. All pregnancies have a background risk of birth defect, loss or other adverse outcomes. In the U.S. general population, the estimated background risk of major birth defects and miscarriage in clinically recognized pregnancies is 2 to 4% and 15 to 20%, respectively.

Data

Available data from published observational studies, case series, and case reports over several decades do not suggest an increased risk for major birth defects or miscarriage in pregnant women with rheumatic diseases (such as rheumatoid arthritis, Behçet's disease, or familial Mediterranean fever (FMF)) treated with colchicine at therapeutic doses during pregnancy. Limitations of these data include the lack of randomization and inability to control for confounders such as underlying maternal disease and maternal use of concomitant medications.

8.2 Lactation

Risk Summary

Colchicine is present in human milk (see Data) . Adverse events in breastfed infants have not been reported in the published literature after administration of colchicine to lactating women. There are no data on the effects of colchicine on milk production. The developmental and health benefits of breastfeeding should be considered along with the mother's clinical need for GLOPERBA and any potential adverse effects on the breastfed infant from GLOPERBA or from the underlying maternal condition.

Data

Limited published data from case reports and a small lactation study demonstrate that colchicine is present in breastmilk. A systematic review of literature reported no adverse effects in 149 breastfed children and advised to reconsider breastfeeding if the infant has diarrhea. In a prospective observational cohort study, no gastrointestinal or other symptoms were reported in 38 colchicine exposed breastfed infants.

8.3 Females and Males of Reproductive Potential

Infertility

Case reports and epidemiology studies in human male subjects on colchicine therapy indicate that infertility from colchicine is rare and may be reversible.

8.4 Pediatric Use

Gout is rare in pediatric patients; safety and effectiveness of GLOPERBA in pediatric patients has not been established.

8.5 Geriatric Use

Because of the increased incidence of decreased renal function in the elderly population, and the higher incidence of other co-morbid conditions in the elderly population requiring the use of other medications, reducing the dosage of colchicine when elderly patients are treated with colchicine should be carefully considered [see Clinical Pharmacology (12.3)] .

8.6 Renal Impairment

No dedicated pharmacokinetic study has been conducted using GLOPERBA in patients with varying degrees of renal impairment. Colchicine is known to be excreted in urine in humans and the presence of severe renal impairment has been associated with colchicine toxicity. Urinary clearance of colchicine and its metabolites may be decreased in patients with impaired renal function. Dose reduction or alternatives should be considered for the prophylaxis of gout flares in patients with severe renal impairment. Colchicine is not effectively removed by hemodialysis. Patients who are undergoing hemodialysis should be monitored carefully for colchicine toxicity.

8.7 Hepatic Impairment

No dedicated pharmacokinetic study using GLOPERBA has been conducted in patients with varying degrees of hepatic impairment. Colchicine is known to be metabolized in humans and the presence of severe hepatic impairment has been associated with colchicine toxicity. Hepatic clearance of colchicine may be significantly reduced and plasma half life prolonged in patients with chronic hepatic impairment.

Dose reduction or alternatives should be considered for the prophylaxis of gout flares in patients with severe hepatic impairment.

10 OVERDOSAGE

The dose of colchicine that would induce significant toxicity for an individual is unknown. Fatalities have occurred after ingestion of a dose as low as 7 mg over a four day period, while other patients have survived after ingesting more than 60 mg. A review of 150 patients who overdosed on colchicine found that those who ingested less than 0.5 mg/kg survived and tended to have milder adverse reactions such as gastrointestinal symptoms, whereas those who took 0.5 to 0.8 mg/kg had more severe adverse reactions, including myelosuppression. There was 100% mortality in those who ingested more than 0.8 mg/kg.

- The first stage of acute colchicine toxicity typically begins within 24 hours of ingestion and includes gastrointestinal symptoms such as abdominal pain, nausea, vomiting, diarrhea and significant fluid loss, leading to volume depletion. Peripheral leukocytosis may also be seen.
- Life threatening complications occur during the second stage, which occurs 24 to 72 hours after drug administration, attributed to multiorgan failure and its consequences. Death is usually a result of respiratory depression and cardiovascular collapse. If the patient survives, recovery of multiorgan injury may be accompanied by rebound leukocytosis and alopecia starting about one week after the initial ingestion.
- Treatment of colchicine poisoning should begin with gastric lavage and measures to prevent shock. Otherwise, treatment is symptomatic and supportive. No specific antidote is known. Colchicine is not effectively removed by hemodialysis [see Clinical Pharmacology (12.3)] .

11 DESCRIPTION

Colchicine is an alkaloid obtained from various species of Colchicum. The chemical name for colchicine is (S)- N-(5,6,7,9-tetrahydro- 1,2,3,10-tetramethoxy-9-oxobenzo[ a]heptalen-7-yl) acetamide with a molecular formula of C22H25NO6and a molecular weight of 399.4.

The structural formula of colchicine is provided in Figure 1.

Figure 1: Colchicine Structural Formula

Colchicine consists of pale yellow scales or powder; it darkens on exposure to light. Colchicine is soluble in water, freely soluble in alcohol, and slightly soluble in ether.

GLOPERBA is supplied for oral administration as a slightly hazy, red liquid with a cherry odor, containing 0.6 mg/5 mL of the active ingredient colchicine USP. Inactive ingredients: benzyl alcohol, FD&C Red No. 40, artificial cherry flavor, anhydrous citric acid, dibasic sodium phosphate, glycerin, propylene glycol, sucralose, xanthan gum and purified water.

12 CLINICAL PHARMACOLOGY

12.1 Mechanism of Action

Colchicine's effectiveness as a prophylactic treatment for gout has been postulated to be due to its ability to block neutrophil mediated inflammatory responses induced by monosodium urate crystals in synovial fluid. Colchicine disrupts the polymerization of β-tubulin into microtubules, thereby preventing the activation, degranulation and migration of neutrophils to sites of inflammation. Colchicine also interferes with the inflammasome complex found in neutrophils and monocytes that mediates interleukin-1β (IL-1β) activation.

12.2 Pharmacodynamics

The pharmacodynamics of colchicine are unknown.

12.3 Pharmacokinetics

Absorption

In healthy adults, GLOPERBA reached a mean Cmaxof 2.16 ± 0.87 ng/mL in 1 hour (range 0.5 to 2 hours) after a single dose administered under fasting conditions. A minimal food effect was observed when GLOPERBA was administered following a high fat, high calorie meal. A slight decrease in Cmaxwas observed; however, the overall extent of absorption based on AUC0-tand AUC0-inf, was similar in the fed and fasted states. The absolute bioavailability of colchicine is reported to be approximately 45%. Mean pharmacokinetic parameter values for GLOPERBA in healthy adults are shown in Table 1.

Table 1: Mean Pharmacokinetic Parameter Estimates for GLOPERBA in Healthy Adults
Parameter | GLOPERBA, 0.6 mg (0.12 mg/mL, 5 mL) Fasted (N=34) | GLOPERBA, 0.6 mg (0.12 mg/mL, 5 mL) Fed (N=34)
Cmax(ng/mL) | 2.16 (0.87) | 1.68 (0.39)
AUC0-t(h∙ng/mL) | 18.59 (4.64) | 17.20 (4.23)
AUC0-inf(h∙ng/mL) | 19.90 (4.74) | 18.47 (4.29)
Tmax(h) (Min-Max) | 1.00 (0.50: 2.00) | 2.00 (1.00: 4.00)
t1/2(h) | 31.04 (5.99) | 30.54 (5.22)

Distribution

The mean apparent volume of distribution (Vz/F) of GLOPERBA in healthy adults was approximately 1420 L. Colchicine binding to serum protein is reported to be low (39%) primarily due to albumin regardless of concentration.

Colchicine crosses the placenta (plasma levels in the fetus are reported to be approximately 15% of the maternal concentration) [see Use in Specific Populations (8.1)] . Colchicine also distributes into breast milk at concentrations similar to those found in the maternal serum [see Use in Specific Populations (8.2)] .

Metabolism

In vitrostudies using human liver microsomes have shown that CYP3A4 is involved in the metabolism of colchicine to 2- O-demethylcolchicine (2-DMC) and 3- O-demethylcolchicine (3-DMC). Glucuronidation is also believed to be a metabolic pathway for colchicine.

Elimination

The mean elimination half-life of GLOPERBA in healthy adults is 31 hours (± 6 hours). In a published study in healthy adults approximately 40 to 65% of a single 1-mg oral dose of colchicine was reported to be recovered unchanged in urine. Enterohepatic recirculation and biliary excretion are postulated to play a role in colchicine elimination. Colchicine is also a substrate of P-gp, and P-gp efflux is postulated to play an important role in colchicine disposition.

Specific Populations

There is no difference between men and women in the pharmacokinetic disposition of colchicine.

Pediatric Patients:Pharmacokinetics of colchicine were not evaluated in pediatric patients.

Geriatric Patients:Pharmacokinetics of GLOPERBA have not been determined in elderly patients. A published report described the pharmacokinetics of a 1 mg oral colchicine tablet dose in four elderly women compared to six young healthy males. The mean age of the four elderly women was 83 years (range 75 to 93), mean weight was 47 kg (38 to 61 kg) and mean creatinine clearance was 46 mL/minute (range 25 to 75 mL/minute). Mean peak plasma levels and AUC of colchicine were two times higher in elderly subjects compared to young healthy males. It is possible that the higher exposure in the elderly subjects was due to decreased renal function.

Patients with Renal Impairment:Pharmacokinetics of colchicine in patients with mild and moderate renal impairment is not known. A published report described the disposition of colchicine (1 mg) in young adult men and women patients who had end stage renal disease requiring dialysis compared to patients with normal renal function. Patients with end stage renal disease had 75% lower colchicine clearance (0.17 vs. 0.73 L/hr/kg) and prolonged plasma elimination half-life (18.8 hours vs. 4.4 hours) as compared to subjects with normal renal function [see Use in Specific Populations (8.6)] .

Patients with Hepatic Impairment:Published reports on the pharmacokinetics of intravenous colchicine in patients with severe chronic liver disease, as well as those with alcoholic or primary biliary cirrhosis, and normal renal function suggest wide inter-patient variability. In some subjects with mild to moderate cirrhosis, the clearance of colchicine is significantly reduced and plasma half-life prolonged compared to healthy subjects. In subjects with primary biliary cirrhosis, no consistent trends were noted [see Use in Specific Populations (8.7)] . No pharmacokinetic data are available for patients with severe hepatic impairment (Child Pugh C).

Drug Interactions

Pharmacokinetics studies evaluating changes in systemic levels of colchicine when co-administered with CYP3A4 and P-gp inhibitors in healthy subjects have been conducted with GOLPERBA. Carvedilol 20 to 40 mg QD (considered a P-gp inhibitor), amlodipine 5 to 10 mg QD (considered a weak inhibitor of CYP3A4) and ciprofloxacin 500 mg BID (considered a moderate CYP3A4 inhibitor) did not cause any significant changes in colchicine systemic levels. Co-administration with posaconazole 300 mg QD (considered a strong CYP3A4 inhibitor) increased AUC by approximately 3-fold.

These results should not be extrapolated to other inhibitors as colchicine is known to be a substrate for CYP3A4 and P-gp, and case reports of colchicine toxicity associated with the co-administration of CYP3A4 and P-gp inhibitors (i.e., clarithromycin) have been published.

Fatal drug interactions have been reported when colchicine is administered with clarithromycin, a dual inhibitor of CYP3A4 and P-gp. Toxicities have also been reported when colchicine is administered with inhibitors of CYP3A4 that may not be potent inhibitors of P-gp (e.g., grapefruit juice), or inhibitors of P-gp that may not be potent inhibitors of CYP3A4 (e.g., cyclosporine). If treatment with a P-gp and CYP3A4 inhibitor is required in patients with normal renal and hepatic function, the patients' dose of colchicine may need to be reduced or interrupted.

13 NONCLINICAL TOXICOLOGY

13.1 Carcinogenesis, Mutagenesis, Impairment of Fertility

Carcinogenesis

Carcinogenicity studies of colchicine have not been conducted. Due to the potential for colchicine to produce aneuploid cells (cells with an unequal number of chromosomes), colchicine presents a theoretical increased risk of malignancy.

Mutagenesis

Colchicine was negative for mutagenicity in the bacterial reverse mutation assay. In a chromosomal aberration assay in cultured human white blood cells, colchicine treatment resulted in the formation of micronuclei. Since published studies demonstrated that colchicine induces aneuploidy from the process of mitotic nondisjunction without structural DNA changes, colchicine is not considered clastogenic, although micronuclei are formed.

Impairment of Fertility

There were no studies conducted of the effects of GLOPERBA on fertility. Published nonclinical studies have demonstrated that colchicine induced disruption of microtubule formation affects meiosis and mitosis. Published colchicine reproductive studies have reported abnormal sperm morphology and reduced sperm counts in males and interference with sperm penetration, second meiotic division and normal cleavage in females.

14 CLINICAL STUDIES

The evidence for the efficacy of colchicine in patients with chronic gout is derived from the published literature. Two randomized clinical trials assessed the efficacy of colchicine 0.6 mg twice a day for the prophylaxis of gout flares in patients with gout initiating treatment with urate-lowering therapy. In both trials, treatment with colchicine decreased the frequency of gout flares.

16 HOW SUPPLIED/STORAGE AND HANDLING

16.1 How Supplied

GLOPERBA (colchicine) Oral Solution is a slightly hazy, red liquid with a cherry odor and the strength of 0.6 mg/5 mL. GLOPERBA (150 mL) is provided in a white, oblong, high density polyethylene bottle with a child-resistant cap.

150 mL: NDC 69557-222-01

16.2 Storage

Store at 20°-25°C (68° - 77°F); excursions permitted to 15°-30°C (59°-86°F). [See USP Controlled Room Temperature.]

17 PATIENT COUNSELING INFORMATION

Advise the patient to read the FDA approved patient labeling (Medication Guide).

Dosing Instructions

Patients should be advised to take GLOPERBA as prescribed, even if they are feeling better. Patients should not alter the dose or discontinue treatment without consulting with their doctor. If a dose of GLOPERBA is missed, take the dose as soon as possible and then return to the normal dosing schedule. However, if a dose is skipped the patient should not double the next dose.

Advise patients and caregivers to measure GLOPERBA with an accurate milliliter measuring device. A household teaspoon is not an accurate measuring device. Advise patients and caregivers to ask their pharmacist to recommend an appropriate measuring device and for instructions for measuring the correct dose.

Fatal Overdose

Instruct patient that fatal overdoses, both accidental and intentional, have been reported in adults and children who have ingested colchicine. GLOPERBA should be kept out of the reach of children.

Blood Dyscrasias

Patients should be informed that bone marrow depression with agranulocytosis, aplastic anemia and thrombocytopenia may occur with GLOPERBA.

Drug and Food Interactions

Advise patients that many drugs or other substances may interact with GLOPERBA and some interactions could be fatal. Therefore, patients should report to their healthcare provider all of the current medications they are taking and check with their healthcare provider before starting any new medications, including short term medications such as antibiotics. Patients should also be advised to report the use of nonprescription medication or herbal products. Grapefruit and grapefruit juice may also interact and should not be consumed during GLOPERBA treatment.

Neuromuscular Toxicity

Patients should be informed that muscle pain or weakness, tingling or numbness in fingers or toes may occur with GLOPERBA alone or when it is used with certain other drugs. Patients developing any of these signs or symptoms must discontinue GLOPERBA and seek medical evaluation immediately.

Infertility

Advise males of reproductive potential that GLOPERBA may rarely and transiently impair fertility [see Use in Specific Populations (8.3)] .

Rx ONLY

Manufactured for:
SCILEX Pharmaceuticals, Inc.
Palo Alto, California
Rev 03/23
GL0-00052

MEDICATION GUIDE

GLOPERBA®(Glow per' bah)
(colchicine) Oral Solution

What is the most important information I should know about GLOPERBA?

GLOPERBA can cause serious side effects or death if levels of GLOPERBA are too high in your body.

- Taking certain medicines with GLOPERBA can cause your level of GLOPERBA to be too high, especially if you have kidney or liver problems.
- Tell your healthcare provider about all your medical conditions, including if you have kidney or liver problems. Your dose of GLOPERBA may need to be changed.
- Tell your healthcare provider about all the medicines you take, including prescription and nonprescription medicines, vitamins and herbal supplements.
- Medicines that you take for a short period of time, such as antibiotics, can interact with GLOPERBA and cause serious side effects or death.
- Talk to your healthcare provider or pharmacist before taking any new medicine.

What is GLOPERBA?

GLOPERBA is a prescription medicine used to prevent gout flares in adults.

It is not known if GLOPERBA is safe and effective for the treatment of sudden (acute) gout flares.

GLOPERBA is not a pain medicine, and it should not be taken to treat pain related to other medical conditions unless specifically prescribed for those conditions.

It is not known if GLOPERBA is safe and effective in children.

Do not take GLOPERBA if you:

- have liver or kidney problems and you take certain other medicines, unless directed to by a healthcare provider. Serious side effects, including death, have happened in people even when GLOPERBA is taken as directed.
- have liver and kidney problems.

See " What is the most important information that I should know about GLOPERBA?"

Before taking GLOPERBA, tell your healthcare provider about all of your medical conditions, including if you:

- are pregnant or plan to become pregnant. It is not known if GLOPERBA can harm your unborn baby.
- are breastfeeding or plan to breastfeed. GLOPERBA can pass into your breast milk. Talk to your healthcare provider about the best way to feed your baby if you take GLOPERBA.
- are a malewith a female partner who can become pregnant. Receiving treatment with GLOPERBA may be related to infertility in some men that is reversible when treatment is stopped.

Tell your healthcare provider about all the medicines you take, including prescription, over-the-counter medicines, vitamins, and herbal supplements.

- Using GLOPERBA with certain other medicines can affect each other, causing serious side effects or death.
- Do nottake GLOPERBA with other medicines unless your healthcare provider tells you to.
- Know the medicines you take. Keep a list of your medicines with you to show your healthcare provider and pharmacist each time you get a new medicine.
- Especially tell your healthcare provider if you take:
  - medicines that may affect how your liver works (CYP3A4 inhibitors)
  - a medicine called cyclosporine (Noeral, Gengraf, Sandimmune)
  - cholesterol lowering medicines, or
  - antibiotics

Ask your healthcare provider or pharmacist if you are not sure if you take any of the medicines listed above. This is not a complete list of all the medicines that can affect GLOPERBA.

How should I take GLOPERBA?

- Take GLOPERBA exactly as your healthcare provider tells you to take it. If you are not sure about your dosing, call your healthcare provider.
- Measure GLOPERBA with an accurate milliliter measuring device. A household teaspoon is not an accurate measuring device.Ask your pharmacist to recommend a measuring device and for instructions on how to measure the correct dose.
- GLOPERBA can be taken with or without food.
- If you take too much GLOPERBA, call your healthcare provider or go to the nearest hospital emergency room right away.
- Do not stop taking GLOPERBA unless your healthcare provider tells you.
- If you miss a dose of GLOPERBA, take it as soon as you remember. If it is almost time for your next dose, skip the missed dose. Take the next dose at your regular time. Do not take 2 doses at the same time.

What should I avoid while taking GLOPERBA?

Avoid eating grapefruit or drinking grapefruit juice while taking GLOPERBA. It can increase your chances of having serious side effects.

What are the possible side effects of GLOPERBA?

GLOPERBA can cause serious side effects, including:

See " What is the most important information that I should know about GLOPERBA?"

- Blood problems.Blood problems have happened in some people taking GLOPERBA. Get medical help right away if you have any of these symptoms:

- pale or gray color to your lips, tongue or palms of your hands.
- unusual bleeding or bruising

- feel weak or tired
- increased infections

- Muscle weakness (neuromuscular toxicity).Muscle weakness has happened in some people taking GLOPERBA. Get medical help right away if you have any of these symptoms:

- muscle weakness or pain

- numbness or tingling in your fingers or toes

The most common side effects of GLOPERBA include:

- diarrhea

- nausea

- vomiting

- abdominal (stomach) pain

Tell your healthcare provider if you have any side effect that bothers you or that does not go away.

These are not all of the possible side effects of GLOPERBA. Call your doctor for medical advice about side effects. You may report side effects to FDA at 1-800-FDA-1088.

How should I store GLOPERBA?

- Store GLOPERBA between 20°-25°C (68° - 77°F); excursions permitted to 15°-30°C (59°-86°F). [See USP Controlled Room Temperature.]

Keep GLOPERBA and all medicines out of the reach of children.

General information about the safe and effective use of GLOPERBA.

Medicines are sometimes prescribed for purposes other than those listed in a Medication Guide. Do not use GLOPERBA for a condition for which it was not prescribed. Do not give GLOPERBA to other people, even if they have the same symptoms that you have. It may harm them.

If you would like more information, talk with your healthcare provider. You can ask your healthcare provider or pharmacist for information about GLOPERBA that is written for healthcare professionals.

What are the ingredients in GLOPERBA?

Active Ingredient:colchicine

Inactive Ingredients:benzyl alcohol, FD&C Red No. 40, artificial cherry flavor, anhydrous citric acid, dibasic sodium phosphate, glycerin, propylene glycol, sucralose, xanthan gum and purified water.

Rx ONLY

Manufactured for:
SCILEX Pharmaceuticals, Inc.
Palo Alto, California
For more information, visit scilexholding.com or call 1-866-SCILEX3.

This Medication Guide has been approved by the U.S Food and Drug Administration

Issued: 7/2019

PRINCIPAL DISPLAY PANEL - 150 mL Bottle Carton

NDC 69557-222-01

GLOPERBA®
(colchicine) oral solution

0.6 mg/5 mL

Rx Only

150 mL